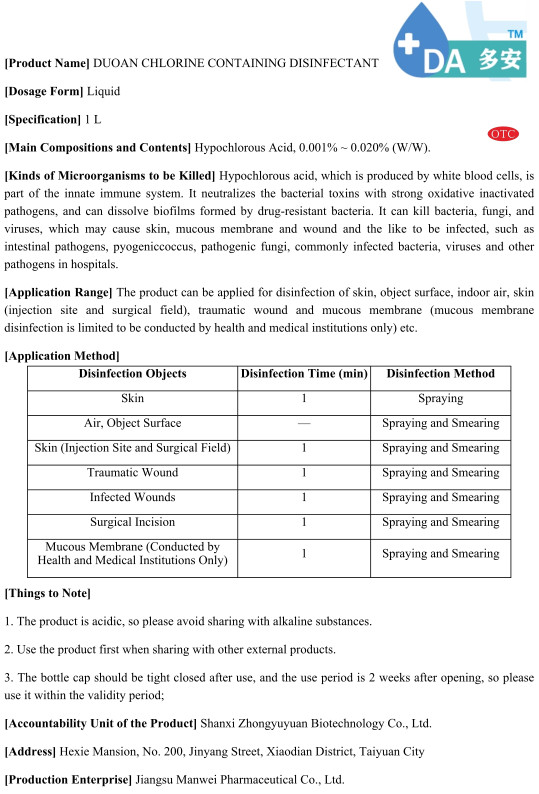 DRUG LABEL: DUOAN CHLORINE CONTAINING DISINFECTANT
NDC: 55117-001 | Form: LIQUID
Manufacturer: Shanxi Zhongyuyuan Biotechnology Co., Lt D.
Category: otc | Type: HUMAN OTC DRUG LABEL
Date: 20200415

ACTIVE INGREDIENTS: SOPHORA FLAVESCENS WHOLE 1.5 g/1 L
INACTIVE INGREDIENTS: ACETIC ACID; WATER

DOSAGE AND ADMINISTRATION

Please do not put it in a dry place.

INACTIVE INGREDIENT

Glacial acetic acid
pure water

INDICATIONS AND USAGE

1.If it is rubbing the skin ,it can use Spraying.

2.If it is rubbing theAir, Object Surface,Skin (Injection Site and Surgical Field),Traumatic Wound,Infected Wounds.Surgical Incision,Mucous Membrane(Conducted by Health and Medical Institutions Only),it can use Spraying and Smearing.

ACTIVE INGREDIENT

Sodium hypochlorite

keep out of children

PURPOSE

Disinfection
Sterilization

WARNINGS

1. The product is acidic, so please avoid sharing with alkaline substances.
2. Use the product first when sharing with other external products.
3. The bottle cap should be tight closed after use, and the use period is 2 weeks after opening, so please use it within the validity period.